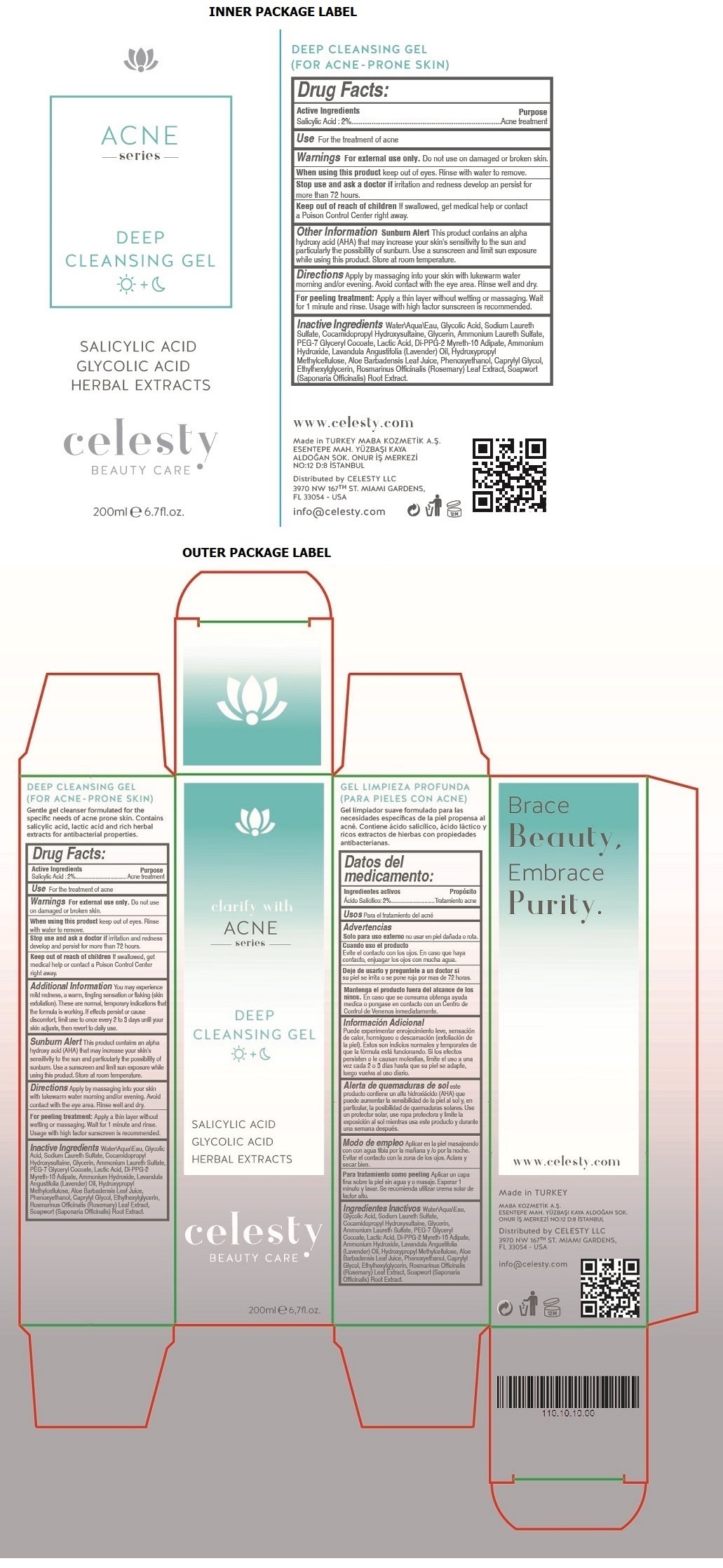 DRUG LABEL: Celesty
NDC: 81120-102 | Form: GEL
Manufacturer: MABA KOZMETIK LIMITED SIRKETI
Category: otc | Type: HUMAN OTC DRUG LABEL
Date: 20201207

ACTIVE INGREDIENTS: SALICYLIC ACID 2 g/100 mL
INACTIVE INGREDIENTS: WATER; GLYCOLIC ACID; SODIUM LAURETH-3 SULFATE; COCAMIDOPROPYL HYDROXYSULTAINE; GLYCERIN; AMMONIUM LAURETH-2 SULFATE; PEG-7 GLYCERYL COCOATE; LACTIC ACID, UNSPECIFIED FORM; DI-PPG-2 MYRETH-10 ADIPATE; AMMONIA; LAVENDER OIL; HYPROMELLOSE, UNSPECIFIED; ALOE VERA LEAF; PHENOXYETHANOL; CAPRYLYL GLYCOL; ETHYLHEXYLGLYCERIN; ROSEMARY; SAPONARIA OFFICINALIS ROOT

celesty ACNE series DEEP CLEANSING GEL

Active Ingredients

Salicylic Acid : 2%

Purpose

Acne treatment

Use

For the treatment of acne

Warnings

For external use only. Do not use on damaged or broken skin.

When using this product keep out of eyes. Rinse with water to remove.

Stop use and ask a doctor if irritation and redness develop and persist for more than 72 hours.

Keep out of reach of children. If swallowed, get medical help or contact a Poison Control Center right away.

Additional Information

You may experience mild redness, a warm, tingling sensation or flaking (skin exfoliation). These are normal, temporary indications that the formula is working. If effects persist or cause discomfort, limit use to once every 2 to 3 days until your skin adjusts, then revert to daily use.

Sunburn Alert This product contains an alpha hydroxy acid (AHA) that may increase your skin's sensitivity to the sun and particularly the possibility of sunburn. Use a sunscreen and limit sun exposure while using this product. Store at room temperature.

Directions

Apply by massaging into your skin with lukewarm water morning and/or evening. Avoid contact with the eye area. Rinse well and dry.

For peeling treatment: Apply a thin layer without wetting or massaging. Wait for 1 minute and rinse. Usage with high factor sunscreen is recommended.

Inactive Ingredients

Water\Aqua\Eau, Glycolic Acid, Sodium Laureth Sulfate, Cocamidopropyl Hydroxysultaine, Glycerin, Ammonium Laureth Sulfate, PEG-7 Glyceryl Cocoate, Lactic Acid, Di-PPG-2 Myreth-10 Adipate, Ammonium Hydroxide, Lavandula Angustifolia (Lavender) Oil, Hydroxypropyl Methylcellulose, Aloe Barbadensis Leaf Juice, Phenoxyethanol, Caprylyl Glycol, Ethylhexylglycerin, Rosmarinus Officinalis (Rosemary) Leaf Extract, Soapwort (Saponaria Officinalis) Root Extract

clarify with ACNE series

SALICYLIC ACID

GLYCOLIC ACID

HERBAL EXTRACTS

BEAUTY CARE

(FOR ACNE - PRONE SKIN)

Gentle gel cleanser formulated for the specific needs of acne prone skin. Contains salicylic acid, lactic acid and rich herbal extracts for antibacterial properties.

Brace Beauty, Embrace Purity.

www.celesty.com

Made in TURKEY

MABA KOZMETIK A.S.

ESENTEPE MAH. YUZBASI KAYA ALDOGAN SOK.

ONUR IS MERKEZI NO:12 D:8 ISTANBUL

Distributed by CELESTY LLC

3970 NW 167TH ST. MIAMI GARDENS,

FL 33054 - USA

info@celesty.com